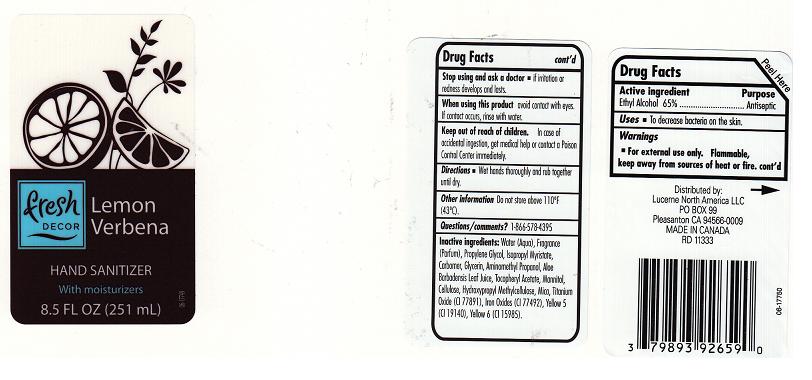 DRUG LABEL: FRESH DECOR
NDC: 21130-462 | Form: LIQUID
Manufacturer: SAFEWAY INC.
Category: otc | Type: HUMAN OTC DRUG LABEL
Date: 20111215

ACTIVE INGREDIENTS: ALCOHOL 65.0 mL/100 mL
INACTIVE INGREDIENTS: WATER; PROPYLENE GLYCOL; ISOPROPYL MYRISTATE; CARBOMER 934; GLYCERIN; AMINOMETHYLPROPANOL; ALOE VERA LEAF; ALPHA-TOCOPHEROL ACETATE; MANNITOL; ALPHA CELLULOSE; HYPROMELLOSE 2208 (15000 MPA.S); MICA; TITANIUM DIOXIDE; FERRIC OXIDE YELLOW; FD&C YELLOW NO. 5; FD&C YELLOW NO. 6

DRUG FACTS

ACTIVE INGREDIENT

ETHYL ALCOHOL 65%

PURPOSE

ANTISEPTIC

USES

TO DECREASE BACTERIA ON THE SKIN.

WARNINGS

FOR EXTERNAL USE ONLY. FLAMMABLE, KEEP AWAY FROM SOURCES OF HEAT OR FIRE.

STOP USING AND ASK A DOCTOR

IF IRRITATION OR REDNESS DEVELOPS AND LASTS.

WHEN USING THIS PRODUCT

AVOID CONTACT WITH EYES. IF CONTACT OCCURS, RINSE WITH WATER.

KEEP OUT OF REACH OF CHILDREN

IN CASE OF ACCIDENTAL INGESTION, GET MEDICAL HELP OR CONTACT A POISON CONTROL CENTER IMMEDIATELY.

DIRECTIONS

WET HANDS THOROUGHLY AND RUB TOGETHER UNTIL DRY.

OTHER INFORMATION

DO NOT STORE ABOVE 110F (43C).

QUESTIONS/COMMENTS?

1-866-578-4395

INACTIVE INGREDIENTS:

WATER (AQUA), FRAGRANCE (PARFUM), PROPYLENE GLYCOL, ISOPROPYL MYRISTATE, CARBOMER, GLYCERIN, AMINOMETHYL PROPANOL, ALOE BARBADENSIS LEAF JUICE, TOCOPHERYL ACETATE, MANNITOL, CELLULOSE, HYDROXYPROPYL METHYLCELLULOSE, MICA, TITANIAM OXIDE (CI 77891), IRON OXIDES (CI 77492), YELLOW 5 (CI 19140), YELLOW 6 (CI 15985).